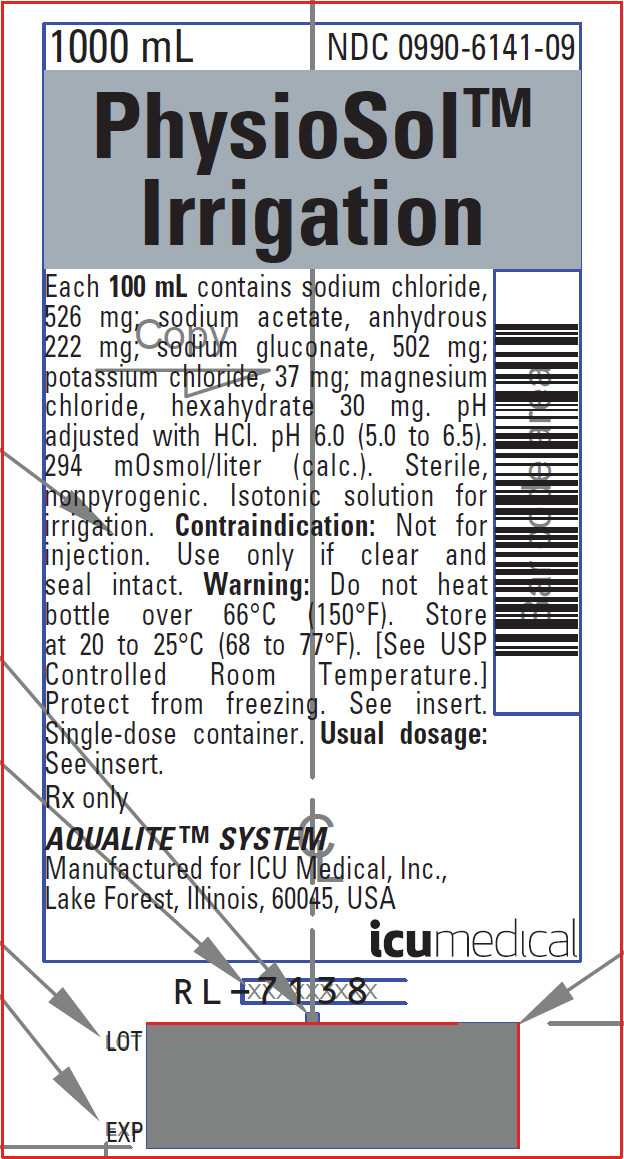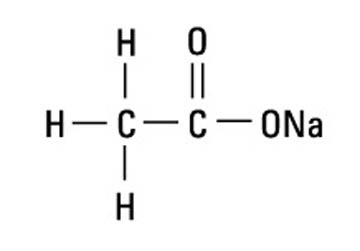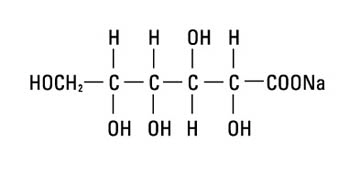 DRUG LABEL: Physiosol
NDC: 0990-6141 | Form: IRRIGANT
Manufacturer: ICU Medical Inc.
Category: prescription | Type: HUMAN PRESCRIPTION DRUG LABEL
Date: 20220106

ACTIVE INGREDIENTS: SODIUM CHLORIDE 526 mg/100 mL; SODIUM ACETATE ANHYDROUS 222 mg/100 mL; SODIUM GLUCONATE 502 mg/100 mL; POTASSIUM CHLORIDE 37 mg/100 mL; MAGNESIUM CHLORIDE 30 mg/100 mL
INACTIVE INGREDIENTS: HYDROCHLORIC ACID; WATER

PHYSIOSOLTM IRRIGATION

Balanced Electrolyte Solution for Irrigation

For All General Irrigation, Washing and Rinsing Purposes

Not for Injection By Usual Parenteral Routes

Semi-rigid Irrigation Container

Rx only

DESCRIPTION

PhysioSol™ is a sterile, nonpyrogenic solution of electrolytes in water for injection intended only for sterile irrigation, washing and rinsing purposes.

Each 100 mL of PhysioSol™ Irrigation contains sodium chloride 526 mg, sodium acetate 222 mg, sodium gluconate 502 mg, potassium chloride 37 mg, magnesium chloride hexahydrate 30 mg. The pH is 6.0 (5.0 to 6.5) adjusted with hydrochloric acid. The solution is isotonic (294 mOsmol/liter, calc.) and has the following electrolyte content (mEq/liter): Na^+ 140, K^+ 5, Mg^++ 3, Cl^− 98, HCO3^− 50 alternates (27 as acetate and 23 as gluconate).

It contains no bacteriostat, antimicrobial agent or added buffer (except for pH adjustment) and is intended only for use as single-dose or short procedure irrigation. When smaller volumes are required the unused portion should be discarded.

PhysioSol™ may be classified as a sterile irrigant, wash, rinse and pharmaceutical vehicle.

Magnesium Chloride, USP is chemically designated magnesium chloride hexahydrate (MgCl2 • 6H2O), colorless, odorless flakes or crystals very soluble in water.

Potassium Chloride, USP is chemically designated KCl, a white granular powder freely soluble in water.

Sodium Chloride, USP is chemically designated NaCl, a white crystalline powder freely soluble in water.

Sodium Acetate, USP is chemically designated sodium acetate (C2H3O2Na), colorless crystals or white crystalline powder or flakes very soluble in water. It has the following structural formula:

Sodium gluconate is chemically designated C6H11NaO7, the normal sodium salt of gluconic acid soluble in water. It has the following structural formula:

Water for Injection, USP is chemically designated H2O.

The semi-rigid container is fabricated from a specially formulated polyolefin. It is a copolymer of ethylene and propylene. The container requires no vapor barrier to maintain the proper drug concentrations.

Solutions in contact with the plastic container may leach out certain chemical components from the plastic in very small amounts; however, biological testing was supportive of the safety of the plastic container materials.

Exposure to temperatures above 25°C/77°F during transport and storage will lead to minor losses in moisture content. Higher temperatures lead to greater losses. It is unlikely that these minor losses will lead to clinically significant changes within the expiration period.

CLINICAL PHARMACOLOGY

PhysioSol™ Irrigation exerts a mechanical cleansing action for sterile irrigation of body cavities, tissues or wounds, indwelling urethral catheters and surgical drainage tubes, and for washing, rinsing or soaking surgical dressings, instruments and laboratory specimens. It also serves as a vehicle for drugs used for irrigation or other pharmaceutical preparations.

PhysioSol™ provides an isotonic calcium-free balanced electrolyte irrigation with the same ionic composition as Normosol™-R, a multiple electrolyte solution for I.V. replacement of acute extracellular fluid losses.

PhysioSol™ Irrigation is considered generally compatible with living tissues and organs.

Magnesium chloride in water dissociates to provide magnesium (Mg^++) and chloride (Cl^−) ions. Magnesium is the second most plentiful cation of the intracellular fluids. It is an important cofactor for enzymatic reactions and plays an important role in neurochemical transmission and muscular excitability. Normal plasma concentration ranges from 1.5 to 2.5 or 3.0 mEq/liter. Magnesium is excreted solely by the kidney at a rate proportional to the plasma concentration and glomerular filtration.

Potassium chloride in water dissociates to provide potassium (K^+) and chloride (Cl^−) ions. Potassium is the chief cation of body cells (160 mEq/liter of intracellular water). It is found in low concentration in plasma and extracellular fluids (3.5 to 5.0 mEq/liter in a healthy adult). Potassium plays an important role in electrolyte balance.

Normally about 80 to 90% of the potassium intake is excreted in the urine; the remainder in the stools and to a small extent, in the perspiration. The kidney does not conserve potassium well so that during fasting or in patients on a potassium free diet, potassium loss from the body continues resulting in potassium depletion.

Sodium chloride in water dissociates to provide sodium (Na^+) and chloride (Cl^−) ions. Sodium (Na^+) is the principal cation of the extracellular fluid and plays a large part in the therapy of fluid and electrolyte disturbances. Chloride (Cl^−) has an integral role in buffering action when oxygen and carbon dioxide exchange occurs in the red blood cells. The distribution and excretion of sodium (Na^+) and chloride (Cl^−) are largely under the control of the kidney which maintains a balance between intake and output.

Sodium acetate provides sodium (Na^+) and acetate (CH3COO^−) ions, the latter anion (a source of hydrogen ion acceptors) serving as an alternate source of bicarbonate (HCO3^−) by metabolic conversion in the liver. This has been shown to proceed readily even in the presence of severe liver disease. Thus, acetate anion exerts a mild systemic antiacidotic action that may be advantageous during fluid and electrolyte replacement therapy.

Sodium gluconate provides sodium (Na^+) and gluconate (C6H11O7^−) ions. Although gluconate is a theoretical alternate metabolic source of bicarbonate (HCO3^−) anion, a significant antiacidotic (alkalizing) action has not been established. Thus, the gluconate anion serves primarily to complete the cation-anion balance of the solutions.

Water is an essential constituent of all body tissues and accounts for approximately 70% of total body weight. Average normal adult daily requirement ranges from two to three liters (1.0 to 1.5 liters each for insensible water loss by perspiration and urine production).

Water balance is maintained by various regulatory mechanisms. Water distribution depends primarily on the concentration of electrolytes in the body compartments and sodium (Na^+) plays a major role in maintaining physiologic equilibrium.

INDICATIONS AND USAGE

PhysioSol™ is indicated for all general irrigation, washing and rinsing purposes which permit use of a sterile, nonpyrogenic electrolyte solution.

CONTRAINDICATIONS

NOT FOR INJECTION BY USUAL PARENTERAL ROUTES.

An electrolyte solution should not be used for irrigation during electrosurgical procedures.

WARNINGS

FOR IRRIGATION ONLY. NOT FOR INJECTION.

Irrigating fluids have been demonstrated to enter the systemic circulation in relatively large volumes, thus, those irrigations must be regarded as a systemic drug. Absorption of large amounts can cause fluid and/or solute overloading resulting in dilution of serum electrolyte concentrations, overhydration, congested states or pulmonary edema.

The risk of dilutional states is inversely proportional to the electrolyte concentrations of administered parenteral solutions. The risk of solute overload causing congested states with peripheral and pulmonary edema is directly proportional to the electrolyte concentrations of such solutions.

Do not heat over 66°C (150°F).

PRECAUTIONS

Caution should be observed when a solution is used for continuous irrigation or allowed to "dwell" inside body cavities because of possible absorption into the blood stream and the production of circulatory overload.

Aseptic technique is essential with the use of sterile solutions for irrigation of body cavities, wounds and urethral catheters or for wetting dressings that come in contact with body tissues.

When used as a "pour" irrigation, no part of the contents should be allowed to contact the surface below the outer protected thread area of the semi-rigid wide mouth container. When used for irrigation via irrigation equipment, the administration set should be attached promptly. Unused portions should be discarded and a fresh container of appropriate size used for the start-up of each cycle or repeat procedure. For repeated irrigations of urethral catheters, a separate container should be used for each patient.

Do not administer unless solution is clear, seal is intact, and container is undamaged. Discard unused portion.

Drug Interactions

Additives may be incompatible. Consult with pharmacist, if available. When introducing additives, use aseptic technique, mix thoroughly and do not store.

Carcinogenesis, Mutagenesis, Impairment of Fertility:

Studies with PhysioSol™ Irrigation have not been performed to evaluate carcinogenic potential, mutagenic potential, or effects on fertility.

Nursing Mothers:

Caution should be exercised when PhysioSol™ Irrigation is administered to a nursing woman.

Pregnancy:

Teratogenic Effects: Pregnancy Category C: Animal reproduction studies have not been conducted with PhysioSol™ Irrigation. It is also not known whether PhysioSol™ Irrigation can cause fetal harm when administered to a pregnant woman or can affect reproduction capacity. PhysioSol™ Irrigation should be given to a pregnant woman only if clearly needed.

Pediatric Use:

The safety and effectiveness of PhysioSol™ Irrigation pH 7.4 have not been established. Its limited use in pediatric patients has been inadequate to fully define proper dosage and limitations for use.

Geriatric Use:

Clinical studies of PhysioSol™ Irrigation have not been performed to determine whether patients over 65 years respond differently from younger subjects. Other reported clinical experience has not identified differences in responses between elderly and younger patients. In general, dose selection for an elderly patient should be cautious, reflecting the greater frequency of decreased hepatic, renal, or cardiac function, and of concomitant disease or other drug therapy.

This drug is known to be substantially excreted by the kidney, and the risk of toxic reactions to this drug may be greater in patients with impaired renal function. Because elderly patients are more likely to have decreased renal function, care should be taken in dose selection, and it may be useful to monitor renal function.

ADVERSE REACTIONS

Possible adverse effects arising from the irrigation of body cavities, tissues, or indwelling catheters and tubes are usually avoidable when proper procedures are followed. Displaced catheters or drainage tubes can lead to irrigation or infiltration of unintended structures or cavities. Excessive volume or pressure during irrigation of closed cavities may cause undue distension or disruption of tissues. Accidental contamination from careless technique may transmit infection.

Should any adverse reaction occur, discontinue the irrigant, evaluate the patient, institute appropriate therapeutic countermeasures and save the remainder of the fluid for examination if deemed necessary.

OVERDOSAGE

In the event of overhydration or solute overload, re-evaluate the patient and institute appropriate corrective measures. See WARNINGS, PRECAUTIONS and ADVERSE REACTIONS.

DOSAGE AND ADMINISTRATION

The dose is dependent upon the capacity or surface area of the structure to be irrigated and the nature of the procedure. When used as a vehicle for other drugs, the manufacturer's recommendations should be followed.

Parenteral drug products should be inspected visually for particulate matter and discoloration prior to administration, whenever solution container permits. See PRECAUTIONS.

HOW SUPPLIED

PhysioSolTM Irrigation is supplied in a 1000 mL single-dose semi-rigid irrigation container. (NDC No. 0409-6141-09)

(NDC No. 0990-6141-09)

ICU Medical is transitioning NDC codes from the "0409" to a "0990" labeler code. Both NDC codes are expected to be in the market for a period of time.

Store at 20 to 25°C (68 to 77°F). [See USP Controlled Room Temperature.] Protect from freezing.

Revised: April, 2018

EN-5714

Manufactured for ICU Medical, Inc. Lake Forest, Illinois, 60045, USA

PRINCIPAL DISPLAY PANEL - 1000 mL Bottle Label

1000 mL
NDC 0990-6141-09

PhysioSol™
Irrigation

Each 100 mL contains sodium chloride,
526 mg; sodium acetate, anhydrous
222 mg; sodium gluconate, 502 mg;
potassium chloride, 37 mg; magnesium
chloride, hexahydrate 30 mg. pH
adjusted with HCl. pH 6.0 (5.0 to 6.5).
294 mOsmol/liter (calc.). Sterile,
nonpyrogenic. Isotonic solution for
irrigation. Contraindication: Not for
injection. Use only if clear and
seal intact. Warning: Do not heat
bottle over 66°C (150°F). Store
at 20 to 25°C (68 to 77°F). [See USP
Controlled Room Temperature.]
Protect from freezing. See insert.
Single-dose container. Usual dosage:
See insert.

Rx only

AQUALITE™ SYSTEM

Manufactured for ICU Medical, Inc.,
Lake Forest, Illinois, 60045, USA

icumedical

RL–7138

LOT

EXP